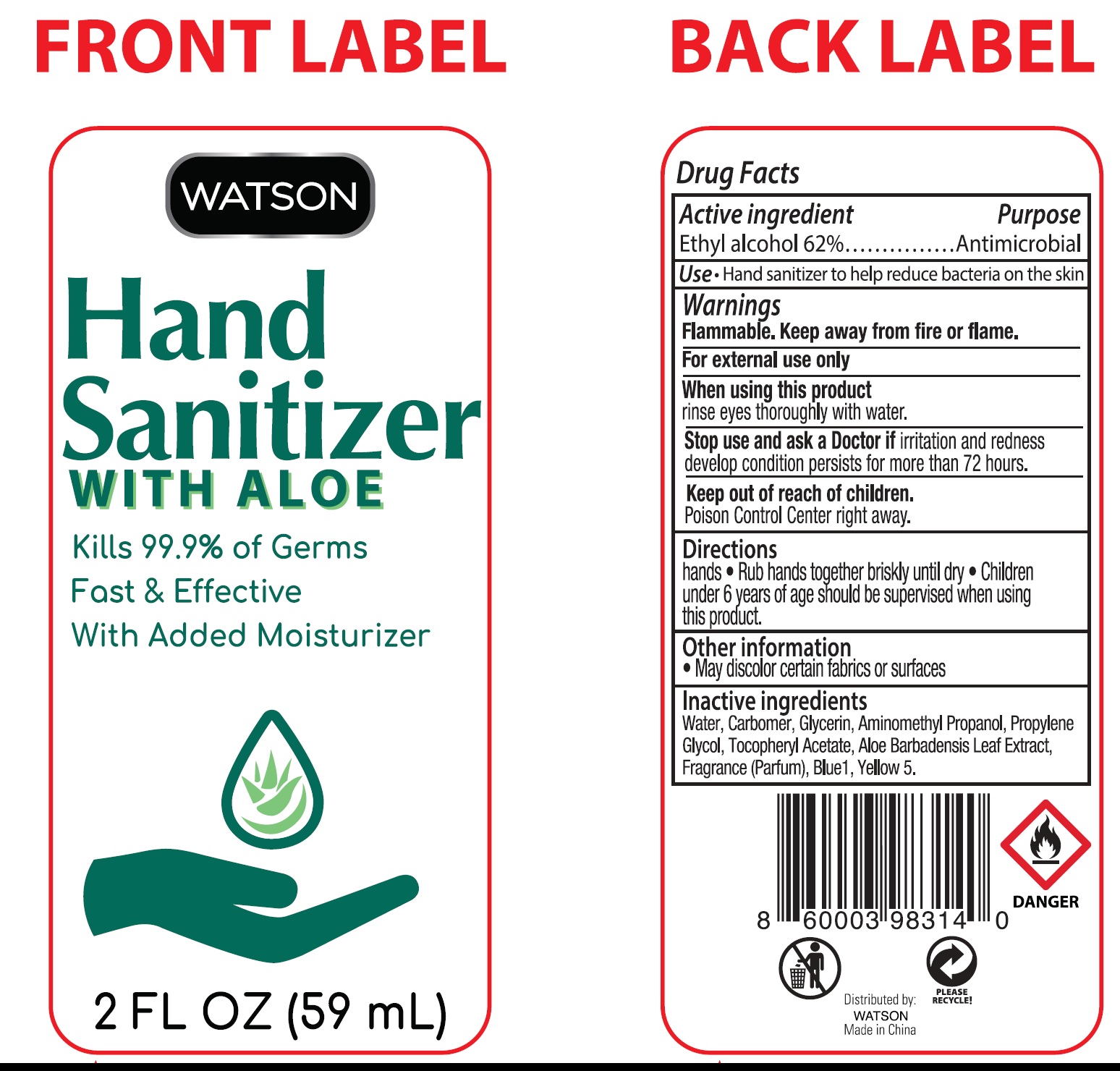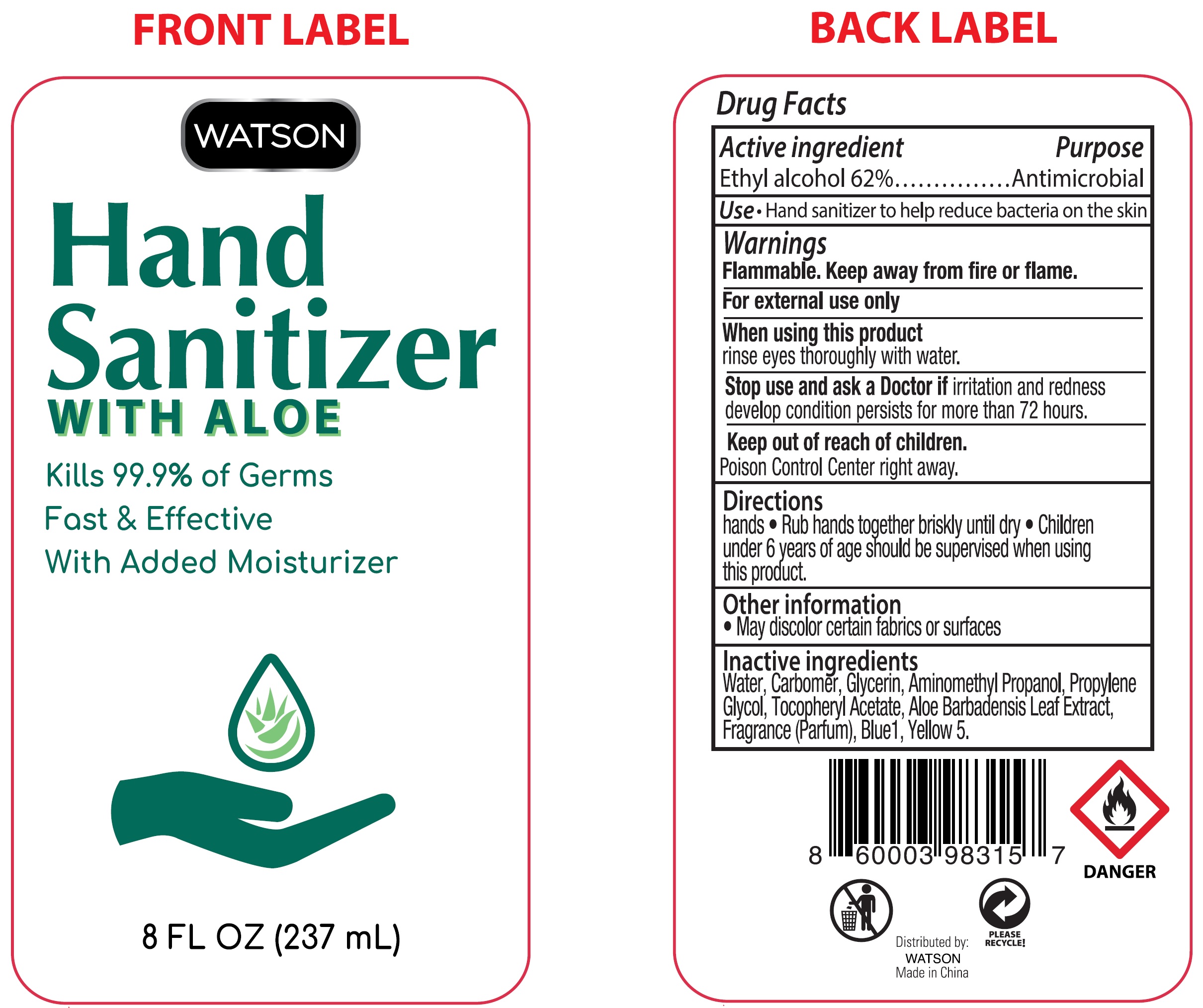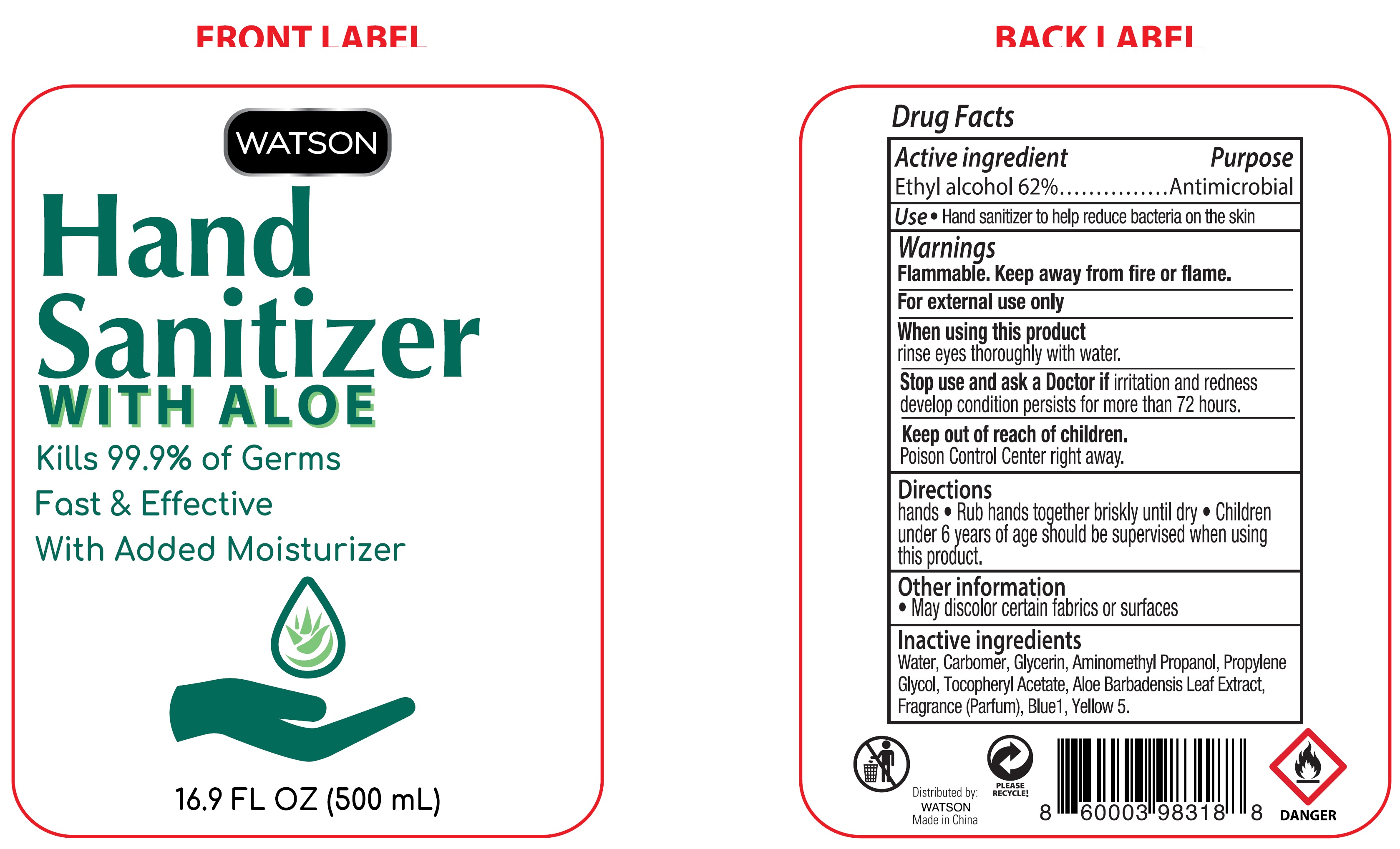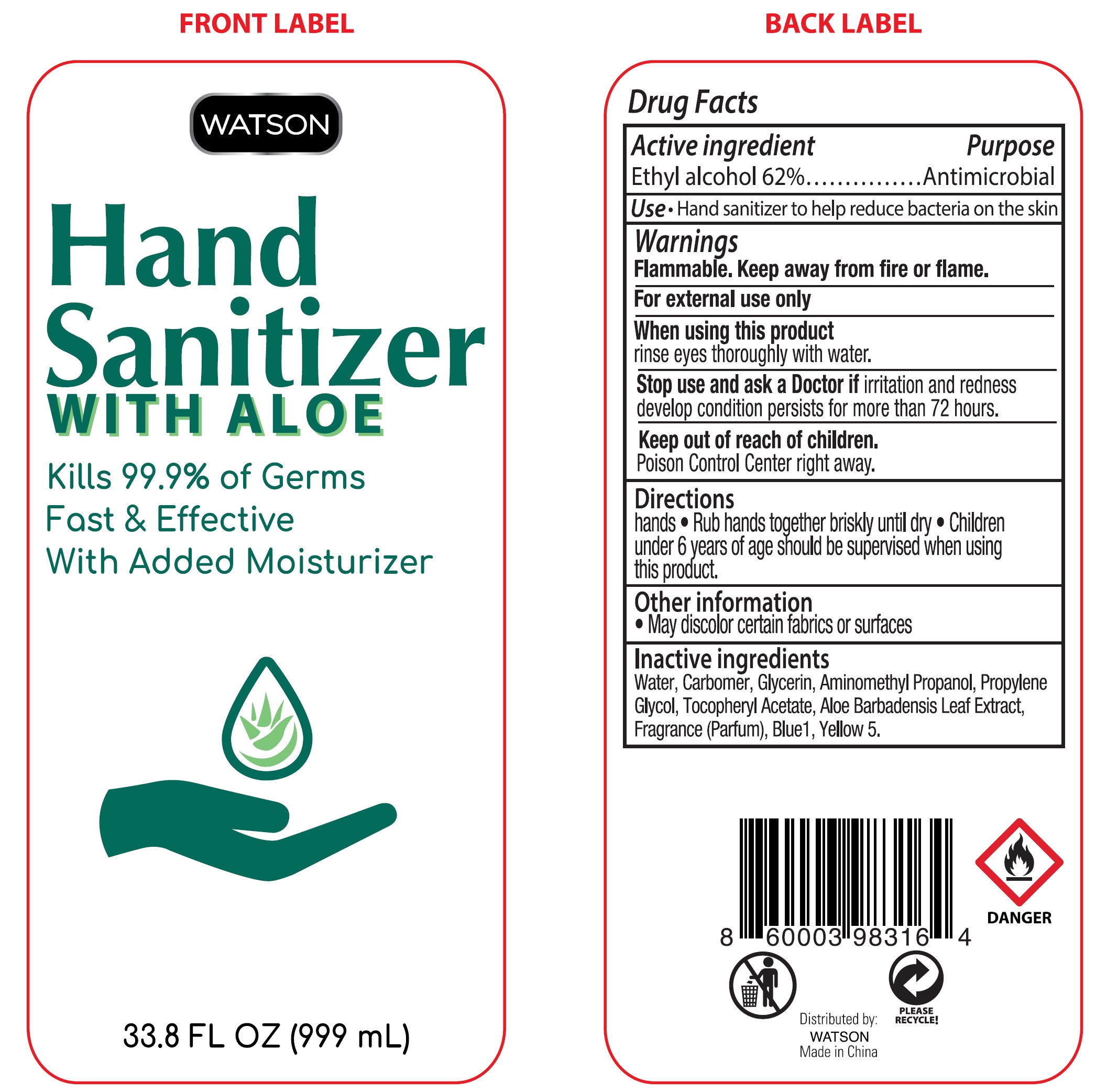 DRUG LABEL: Watson Hand Sanitizer
NDC: 90061-011 | Form: GEL
Manufacturer: Tash Market Place
Category: otc | Type: HUMAN OTC DRUG LABEL
Date: 20220221

ACTIVE INGREDIENTS: ALCOHOL 0.62 mL/1 mL
INACTIVE INGREDIENTS: WATER; CARBOMER HOMOPOLYMER, UNSPECIFIED TYPE; GLYCERIN; AMINOMETHYLPROPANOL; PROPYLENE GLYCOL; .ALPHA.-TOCOPHEROL ACETATE; ALOE VERA LEAF; FD&C BLUE NO. 1

Watson Hand Sanitizer

Active ingredient

Ethyl alcohol 62%

Purpose

Antimicrobial

Use

- Hand sanitizer to help reduce bacteria on the skin

Warnings

Flammable. Keep away from fire or flame.

For external use only

When using this product

rinse eyes thoroughly with water.

Stop use and ask a Doctor

if irritation and redness develop condition persists for more than 72 hours.

Keep out of reach of children.

Poison Control Center right away.

Directions

- Rub hands together briskly until dry.
- Children under 6 years of age should be supervised when using this product.

Other information

- May discolor certain fabrics or surfaces

Inactive ingredients

Water, Carbomer, Glycerin, Aminomethyl Propanol, Propylene Glycol, Tocopheryl Acetate, Barbadensis Leaf Extract, Fragrance (Parfun), Blue 1.